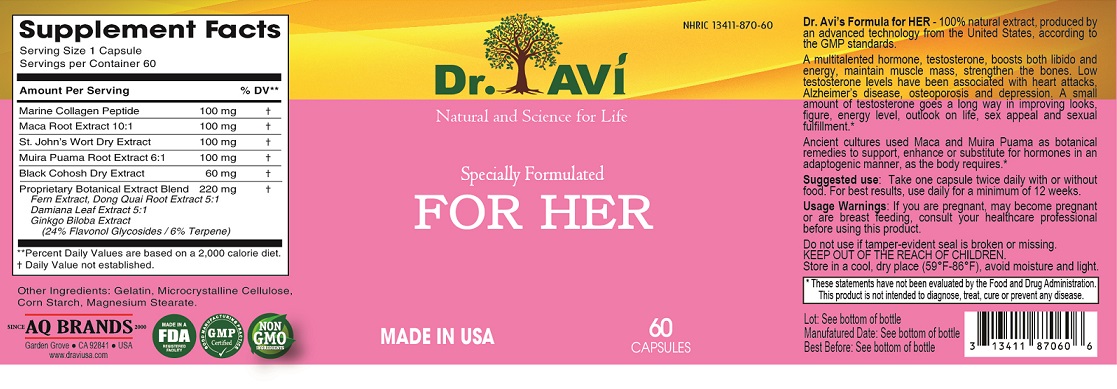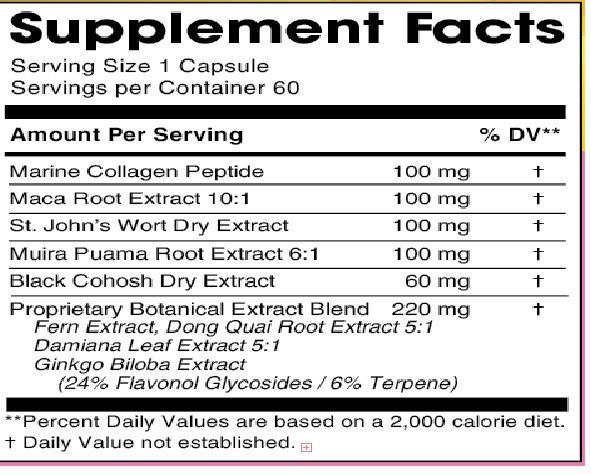 DRUG LABEL: Dr Avi For Her
NDC: 13411-870 | Form: CAPSULE
Manufacturer: Advanced Pharmaceutical Services, Inc. Dba Affordable Quality Pharmaceuticals
Category: other | Type: DIETARY SUPPLEMENT
Date: 20210405

ACTIVE INGREDIENTS: MARINE COLLAGEN, SOLUBLE 100 mg/1 1; LEPIDIUM MEYENII ROOT 100 mg/1 1; ST. JOHN'S WORT 100 mg/1 1; PTYCHOPETALUM OLACOIDES ROOT 100 mg/1 1; BLACK COHOSH 60 mg/1 1; PHLEBODIUM AUREUM LEAF 20 mg/1 1; PHLEBODIUM AUREUM ROOT 20 mg/1 1; ANGELICA SINENSIS ROOT 80 mg/1 1; TURNERA DIFFUSA LEAF 80 mg/1 1; GINKGO 20 mg/1 1
INACTIVE INGREDIENTS: GELATIN, UNSPECIFIED; MICROCRYSTALLINE CELLULOSE; STARCH, CORN; MAGNESIUM STEARATE

Identity

DIETARY SUPPLEMENT

Warning

If you are pregnant, may become pregnant or are breast feeding, consult your healthcare professional before using this product.

Safe handling and warning

Do not use if tamper-evident seal is broken or missing.

Store in a cool, dry place (59°F-86°F), avoid moisture and light.

Health claim

Dr. Avi’s Formula for HER - 100% natural extract, produced by an advanced technology from the United States, according to the GMP standards.
A multitalented hormone, testosterone, boosts both libido and energy, maintain muscle mass, strengthen the bones. Low testosterone levels have been associated with heart attacks, Alzheimer’s disease, osteoporosis and depression. A small amount of testosterone goes a long way in improving looks, figure, energy level, outlook on life, sex appeal and sexual fulfillment.*
Ancient cultures used Maca and Muira Puama as botanical remedies to support, enhance or substitute for hormones in an adaptogenic manner, as the body requires*

* These statements have not been evaluated by the Food & Drug Administration. This product is not intended to diagnose, treat, cure, or prevent any disease.

Direction

Take one capsule twice daily with or without food. For best results, use daily for a minimum of 12 weeks.